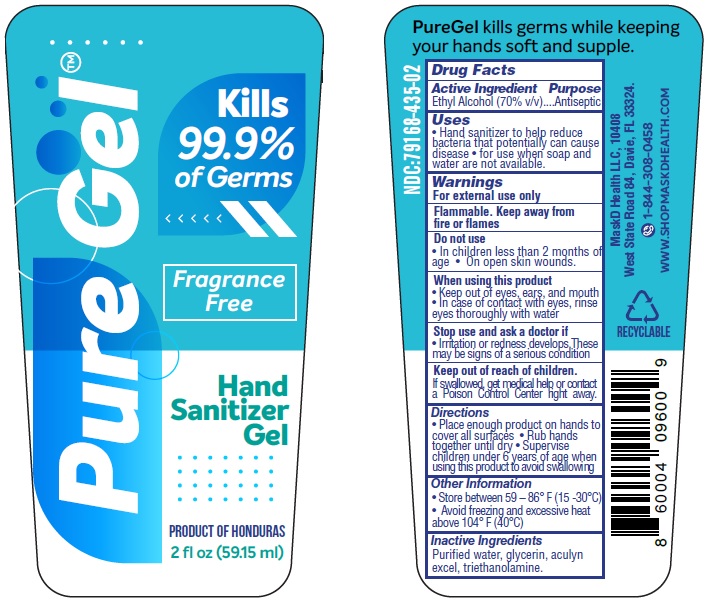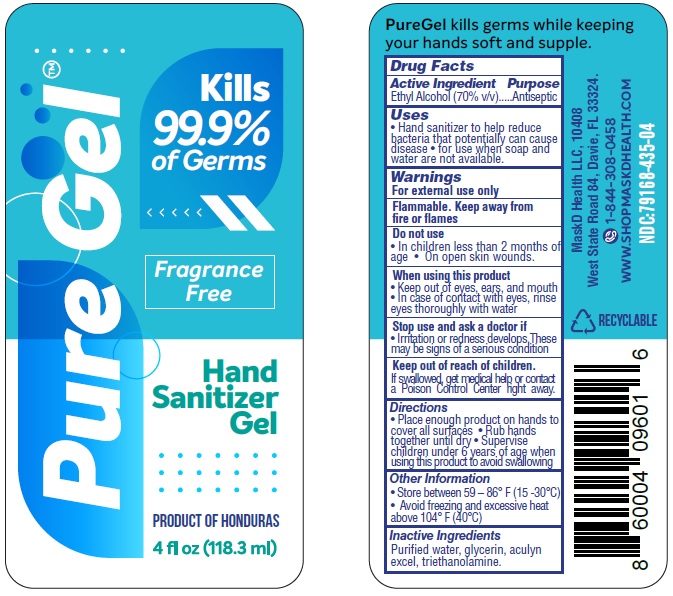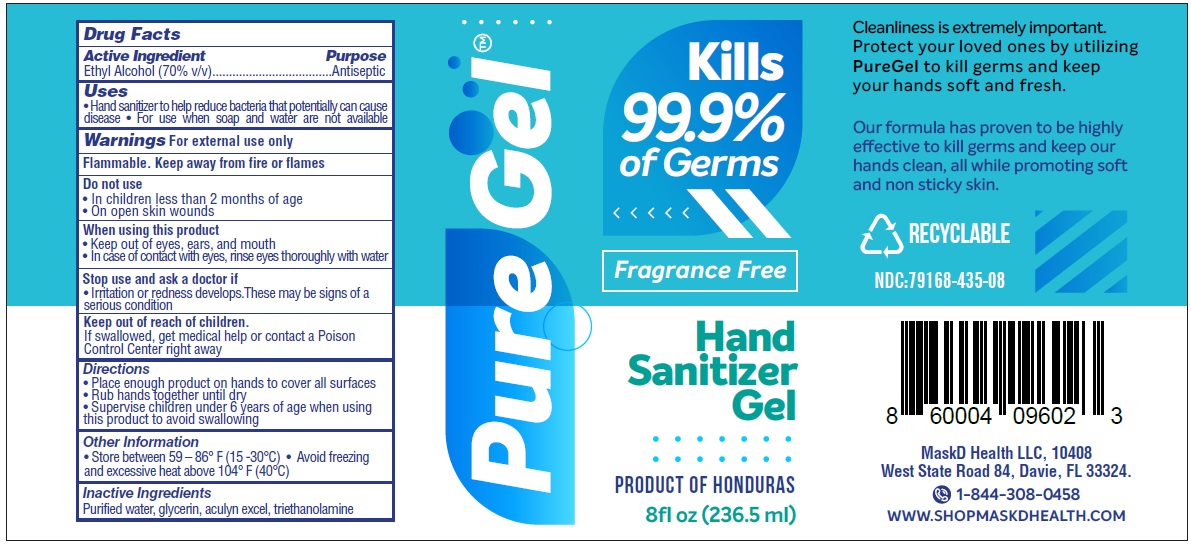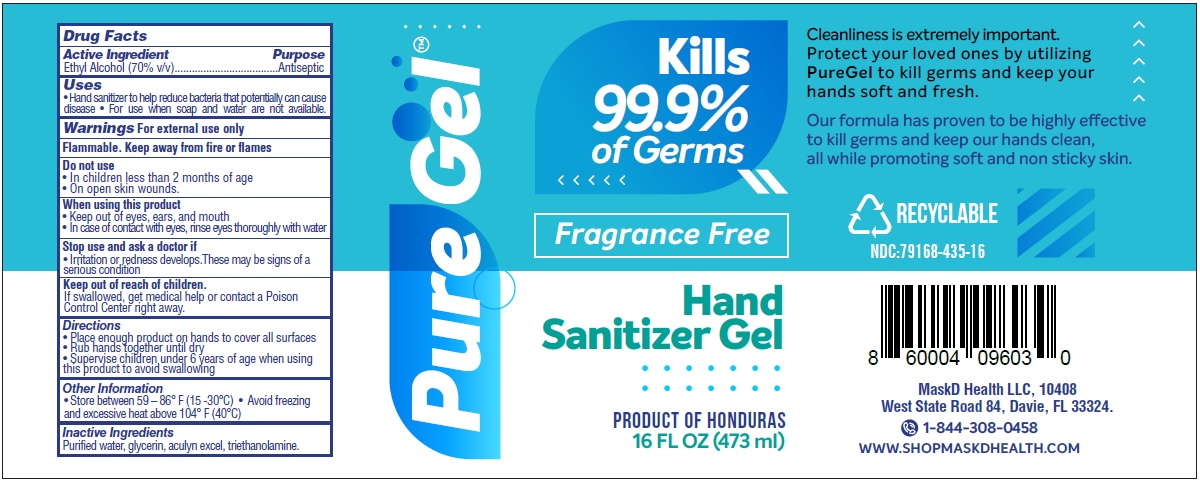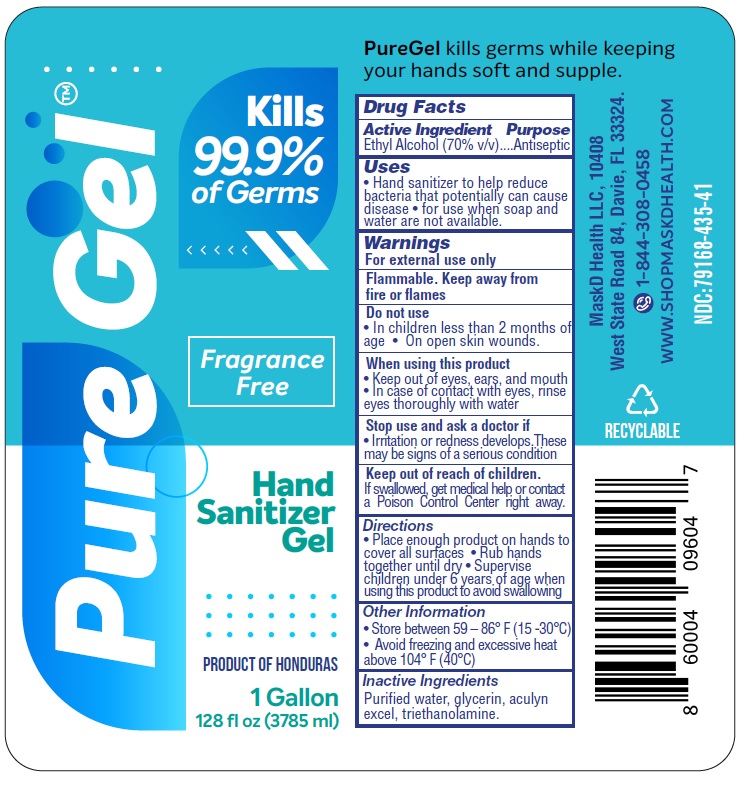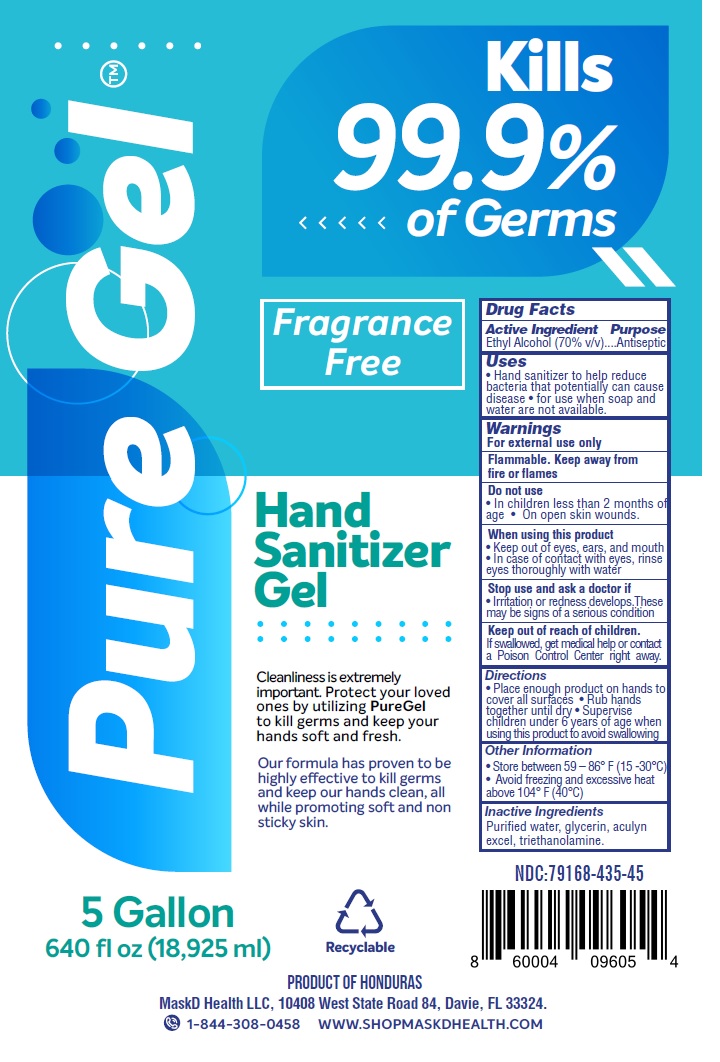 DRUG LABEL: Pure Gel Hand Sanitizer
NDC: 79168-435 | Form: GEL
Manufacturer: American Textile & Apparel Inc.
Category: otc | Type: HUMAN OTC DRUG LABEL
Date: 20200903

ACTIVE INGREDIENTS: ALCOHOL 70 mL/100 mL
INACTIVE INGREDIENTS: WATER; GLYCERIN; ACULYN EXCEL (POLYMER DISPERSION); TROLAMINE

Pure Gel™ Hand Sanitizer Gel

Active Ingredient

Ethyl Alcohol (70% v/v)

Purpose

Antiseptic

Uses

• Hand sanitizer to help reduce bacteria that potentially can cause disease • For use when soap and water are not available.

Warnings

For external use only

Flammable. Keep away from fire or flames

Do not use

• In children less than 2 months of age • On open skin wounds.

When using this product

• Keep out of eyes, ears, and mouth
• In case of contact with eyes, rinse eyes thoroughly with water

Stop use and ask a doctor if

• Irritation or redness develops. These may be signs of a serious condition

Keep out of reach of children.

If swallowed, get medical help or contact a Poison Control Center right away.

Directions

• Place enough product on hands to cover all surfaces • Rub hands together until dry • Supervise children under 6 years of age when using this product to avoid swallowing

Other Information

• Store between 59 – 86° F (15 -30°C)
• Avoid freezing and excessive heat above 104° F (40°C)

Inactive Ingredients

Purified water, glycerin, aculyn excel, triethanolamine.

Kills 99.9% of Germs

PureGel kills germs while keeping your hands soft and supple.

Fragrance Free

PRODUCT OF HONDURAS

Cleanliness is extremely important. Protect your loved ones by utilizing PureGel to kill germs and keep your hands soft and fresh.

Our formula has proven to be highly effective to kill germs and keep our hands clean, all while promoting soft and non sticky skin.

MaskD Health LLC, 10408 West State Road 84, Davie, FL 33324.

1-844-308-0458 WWW.SHOPMASKDHEALTH.COM